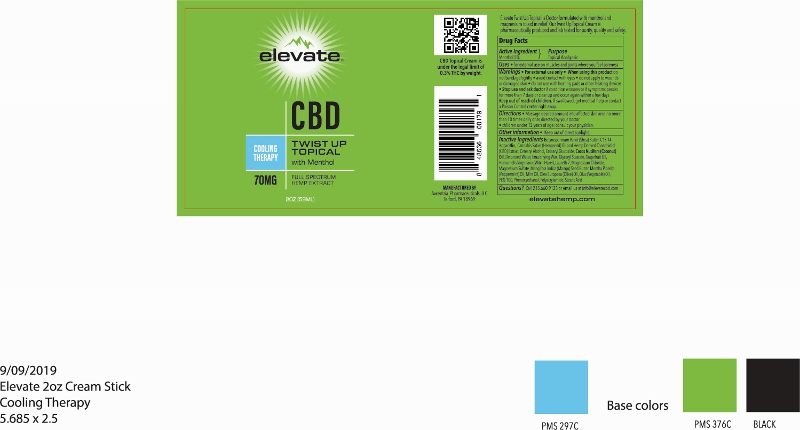 DRUG LABEL: elevate COOLING THERAPY TWIST UP
NDC: 76348-456 | Form: CREAM
Manufacturer: Renu Laboratories, Inc.
Category: otc | Type: HUMAN OTC DRUG LABEL
Date: 20220113

ACTIVE INGREDIENTS: MENTHOL 2.8 g/56 g
INACTIVE INGREDIENTS: PEPPERMINT OIL; WITCH HAZEL; SHEA BUTTER; CANNABIS SATIVA SEED OIL; CANNABIDIOL; PHENOXYETHANOL; OLIVE OIL; COCONUT OIL; MANGIFERA INDICA SEED BUTTER; POLYACRYLAMIDE (10000 MW); CETEARYL GLUCOSIDE; WATER; MAGNESIUM SULFATE, UNSPECIFIED; STEARIC ACID; WHITE WAX; CETOSTEARYL ALCOHOL; GLYCERYL STEARATE/PEG-100 STEARATE; CORN OIL; MAGNESIUM CHLORIDE; C13-14 ISOPARAFFIN; LAURETH-7

elevate COOLING THERAPY TWIST UP

ACTIVE INGREDIENT

Menthol

Stop use and ask doctor if condition worsens or if symptoms persist for more than 7 days or clear up and occur again within a few days.

Keep out of reach of children. If swallowed, get medical help or contact a Poison Control Center right away.

Purpose

Topical Analgesic

QUESTIONS

Questions? Call 215.660.9123 or email us at info@elevatecbd.com

When using this product

- do not bandage tightly
- avoid contact with eyes
- do not apply to wounds or damaged skin
- do not use with heating pads or other heating devices.

Other information

- Keep out of direct sunlight

STATEMENT OF IDENTITY

elevate CBD COOLING THERAPY TWIST UP TOPICAL with Menthol

Uses

- For external use on muscles and joints where you feel soreness

DOSAGE AND ADMINISTRATION

Massage desired amount into affected skin area no more than 10 times daily or as directed by your doctor.

children under 12 years of age consult your physician.

RECENT MAJOR CHANGES

Bullets removed

The word "Directions" was removed

Warnings

- For external use only
- When using this product do not bandage tightly
- avoid contact with eyes
- do not apply to to wounds or damaged skin
- do not use with heating pads or other heating devices

Inactive Ingredients

Butyrospermum Parkii (Shea) Butter, C13-14 Isoparaffin, Cannabis Sativa (Hempseed) Oil and Hemp Derived Cannabidiol (CBD) Extract, Cetearyl Alcohol, Cetearyl Glucoside, Cocos Nucifera (Coconut) Oil, Deionized Water, Emulsifying Wax, Glyceryl Stearate, Grapefruit Oil, Hamamelis Virginiana (Witch Hazel), Laureth-7, Magnesium Chloride, Magnesium Sulfate, Mangifera Indica (Mango) Seed Butter, Mentha Piperita (Peppermint) Oil, Mint Oil, Olea Europaea (Olive) Oil, Olus (Vegetable) Oil, PEG-100, Phenoxyethanol, Polyacrylamide, Stearic Acid

elevate Twist Up Topical label